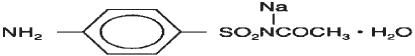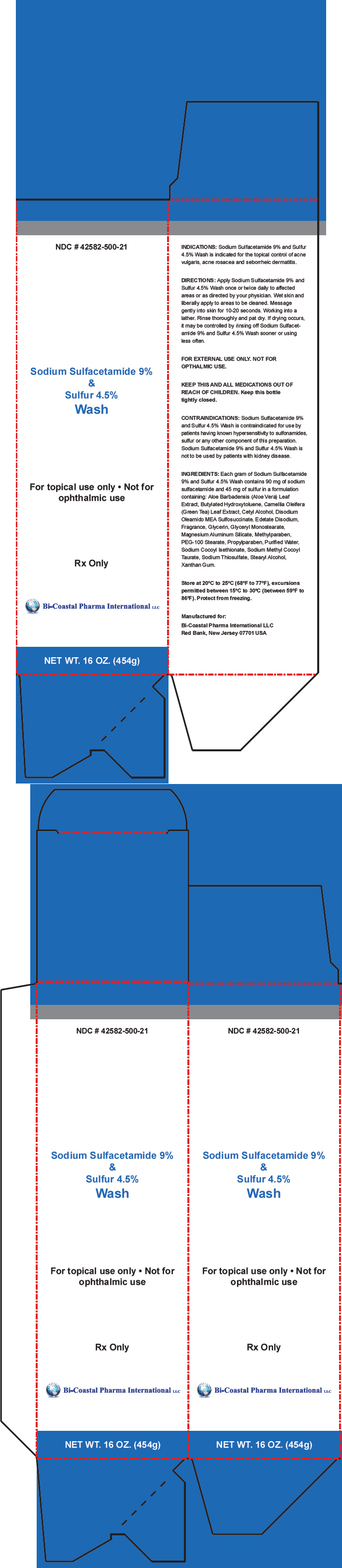 DRUG LABEL: Sulfacetamide Sodium and Sulfur
NDC: 42582-500 | Form: CREAM
Manufacturer: Bi-Coastal Pharma International LLC
Category: prescription | Type: HUMAN PRESCRIPTION DRUG LABEL
Date: 20220118

ACTIVE INGREDIENTS: SULFACETAMIDE SODIUM 90 mg/1 g; SULFUR 45 mg/1 g
INACTIVE INGREDIENTS: ALOE VERA LEAF; BUTYLATED HYDROXYTOLUENE; GREEN TEA LEAF; CETYL ALCOHOL; DISODIUM OLEAMIDO MONOETHANOLAMINE SULFOSUCCINATE; EDETATE DISODIUM; GLYCERIN; GLYCERYL MONOSTEARATE; MAGNESIUM ALUMINUM SILICATE; METHYLPARABEN; PEG-100 STEARATE; PROPYLPARABEN; WATER; SODIUM COCOYL ISETHIONATE; SODIUM METHYL COCOYL TAURATE; SODIUM THIOSULFATE; STEARYL ALCOHOL; XANTHAN GUM

Sodium Sulfacetamide 9% & Sulfur 4.5% Wash

DESCRIPTION

Sulfacetamide sodium is a sulfonamide with antibacterial activity while sulfur acts as a keratolytic agent. Chemically sulfacetamide sodium is N-[(4-aminophenyl) sulfonyI]-acetamide, monosodium salt, monohydrate. The structural formula is:

Each gram of sulfacetamide sodium USP 9% and sulfur USP 4.5% contains 90 mg of Sodium Sulfacetamide USP and 45 mg of Sulfur USP in a cream containing: Aloe Barbadensis (Aloe Vera) Leaf Extract, Butylated Hydroxytoluene, Camellia Oleifera (Green Tea) Leaf Extract, Cetyl Alcohol, Disodium Oleamido MEA Sulfosuccinate, Edetate Disodium, Fragrance, Glycerin, Glyceryl Monostearate, Magnesium Aluminum Silicate, Methylparaben, PEG-100 Stearate, Propylparaben, Purified Water, Sodium Cocoyl Isethionate, Sodium Methyl Cocoyl Taurate, Sodium Thiosulfate, Stearyl Alcohol, Xanthan Gum.

CLINICAL PHARMACOLOGY

The most widely accepted mechanism of action of sulfonamides is the Woods-Fildes theory, which is based on the fact that sulfonamides act as competitive antagonists to para-aminobenzoic acid (PABA), an essential component for bacterial growth. While absorption through intact skin has not been determined, sulfacetamide sodium is readily absorbed from the gastrointestinal tract when taken orally and excreted in the urine, largely unchanged. The biological half-life has variously been reported as 7 to 12.8 hours. The exact mode of action of sulfur in the treatment of acne is unknown, but it has been reported that it inhibits the growth of Propionibacterium acnes and the formation of free fatty acids.

INDICATIONS

Sulfacetamide sodium and sulfur wash is indicated in the topical control of acne vulgaris, acne rosacea and seborrheic dermatitis.

CONTRAINDICATIONS

Sulfacetamide sodium and sulfur wash is contraindicated for use by patients having known hypersensitivity to sulfonamides, sulfur or any other component of this preparation. Sulfacetamide sodium and sulfur wash is not to be used by patients with kidney disease.

WARNINGS

Although rare, sensitivity to sulfacetamide sodium may occur. Therefore, caution and careful supervision should be observed when prescribing this drug for patients who may be prone to hypersensitivity to topical sulfonamides. Systemic toxic reactions such as agranulocytosis, acute hemolytic anemia, purpura hemorrhagica, drug fever, jaundice, and contact dermatitis indicate hypersensitivity to sulfonamides. Particular caution should be employed if areas of denuded or abraded skin are involved.

FOR EXTERNAL USE ONLY. Keep away from eyes. Keep out of reach of children. Keep container tightly closed.

PRECAUTIONS

General

lf irritation develops, use of the product should be discontinued and appropriate therapy instituted. Patients should be carefully observed for possible local irritation or sensitization during longterm therapy. The object of this therapy is to achieve desquamation without irritation, but sulfacetamide sodium and sulfur can cause reddening and scaling of the epidermis. These side effects are not unusual in the treatment of acne vulgaris, but patients should be cautioned about the possibility.

Information for Patients

Avoid contact with eyes, eyelids, lips and mucous membranes. If accidental contact occurs, rinse with water. If excessive irritation develops, discontinue use and consult your physician.

Carcinogenesis, Mutagenesis and Impairment of Fertility

Longterm studies in animals have not been performed to evaluate carcinogenic potential.

Pregnancy

Category C

Animal reproduction studies have not been conducted with sulfacetamide sodium and sulfur lotion. It is also not known whether sulfacetamide sodium and sulfur wash can cause fetal harm when administered to a pregnant woman or can affect reproduction capacity. Sulfacetamide sodium and sulfur wash should be given to a pregnant woman only if clearly needed.

Nursing Mothers

It is not known whether sulfacetamide sodium is excreted in the human milk following topical use of sulfacetamide sodium and sulfur lotion. However, small amounts of orally administered sulfonamides have been reported to be eliminated in human milk. In view of this and because many drugs are excreted in human milk, caution should be exercised when sulfacetamide sodium and sulfur wash is administered to a nursing woman.

Pediatric Use

Safety and effectiveness in children under the age of 12 have not been established.

ADVERSE REACTIONS

Although rare, sulfacetamide sodium may cause local irritation.

DOSAGE AND ADMINISTRATION

Use once daily or as directed by your physician. Wet skin. Apply in a film to entire face, avoiding contact with eyes or mucous membranes. Wait 10 minutes or until dry. Rinse thoroughly with water and pat dry.

HOW SUPPLIED

Sulfacetamide sodium 9% and sulfur 4.5% wash is supplied in
16 oz (454 g) bottle NDC 42582-500-21

STORAGE AND HANDLING

Store at 20°-25°C (68°-77°F), excursions permited between 15°-30°C (59°-86°F). Brief exposure to temperatures up to 40° (104°F) may be tolerated provided the mean kinetic temperature does not exceed 25°C (77°F); however such exposure should be minimized. Protect from freezing.

Call your doctor about side effects. You may report side effects to FDA at 1-800-FDA-1088.

KEEP THIS AND ALL MEDICATIONS OUT OF THE REACH OF CHILDREN

Rx Only

Manufactured for:
Bi-Coastal Pharma International LLC
Red Bank, New Jersey 07701 USA

PRINCIPAL DISPLAY PANEL - 454 g Bottle Carton

NDC # 42582-500-21

Sodium Sulfacetamide 9%
&
Sulfur 4.5%
Wash

For topical use only • Not for
ophthalmic use

Rx Only

Bi-Coastal Pharma International LLC

NET WT. 16 OZ. (454g)